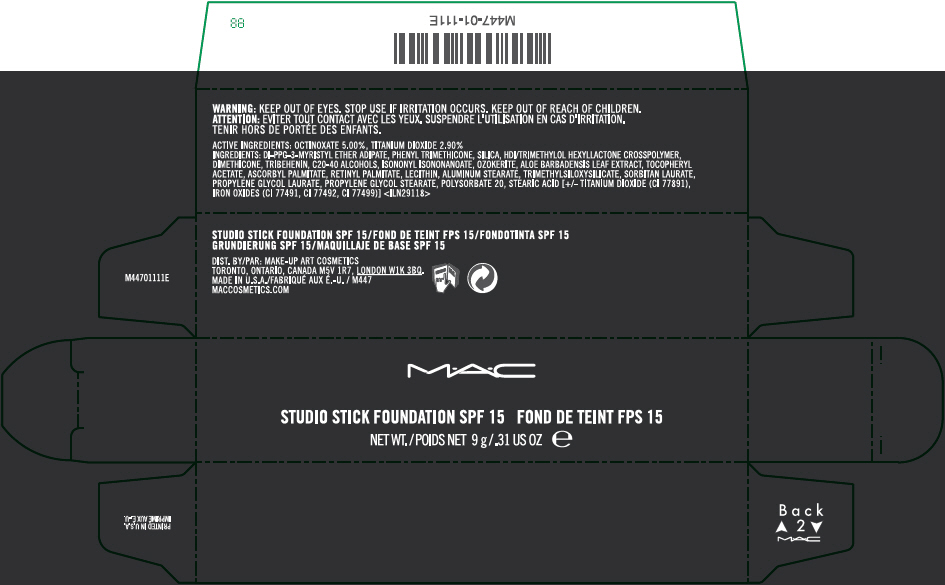 DRUG LABEL: STUDIO FOUNDATION SPF 15
NDC: 40046-0057 | Form: STICK
Manufacturer: MAKEUP ART COSMETICS
Category: otc | Type: HUMAN OTC DRUG LABEL
Date: 20120816

ACTIVE INGREDIENTS: OCTINOXATE 5 g/100 g; TITANIUM DIOXIDE 2.9 g/100 g
INACTIVE INGREDIENTS: DI-PPG-3 MYRISTYL ETHER ADIPATE; PHENYL TRIMETHICONE; SILICON DIOXIDE; DIMETHICONE; TRIBEHENIN; ISONONYL ISONONANOATE; ALOE VERA LEAF; .ALPHA.-TOCOPHEROL ACETATE; ASCORBYL PALMITATE; VITAMIN A PALMITATE; ALUMINUM STEARATE; SORBITAN MONOLAURATE; PROPYLENE GLYCOL MONOLAURATE; PROPYLENE GLYCOL STEARATE; POLYSORBATE 20; STEARIC ACID; FERRIC OXIDE RED; FERRIC OXIDE YELLOW; FERROSOFERRIC OXIDE

STUDIO STICK FOUNDATION SPF 15

WARNING

KEEP OUT OF EYES. STOP USE IF IRRITATION OCCURS. KEEP OUT OF REACH OF CHILDREN.

ACTIVE INGREDIENTS

OCTINOXATE 5.00%, TITANIUM DIOXIDE 2.90%

INGREDIENTS

DI-PPG-3-MYRISTYL ETHER ADIPATE, PHENYL TRIMETHICONE, SILICA, HDI/TRIMETHYLOL HEXYLLACTONE CROSSPOLYMER, DIMETHICONE, TRIBEHENIN, C20-40 ALCOHOLS, ISONONYL ISONONANOATE, OZOKERITE, ALOE BARBADENSIS LEAF EXTRACT, TOCOPHERYL ACETATE, ASCORBYL PALMITATE, RETINYL PALMITATE, LECITHIN, ALUMINUM STEARATE, TRIMETHYLSILOXYSILICATE, SORBITAN LAURATE, PROPYLENE GLYCOL LAURATE, PROPYLENE GLYCOL STEARATE, POLYSORBATE 20, STEARIC ACID [+/- TITANIUM DIOXIDE (CI 77891), IRON OXIDES (CI 77491, CI 77492, CI 77499)] <ILN29118>

DIST. BY/PAR: MAKE-UP ART COSMETICS
TORONTO, ONTARIO, CANADA M5V 1R7, LONDON W1K 3BQ.

PRINCIPAL DISPLAY PANEL - 9 g Tube Carton

M•A•C

STUDIO STICK FOUNDATION SPF 15

NET WT./POIDS NET 9 g/.31 US OZ e